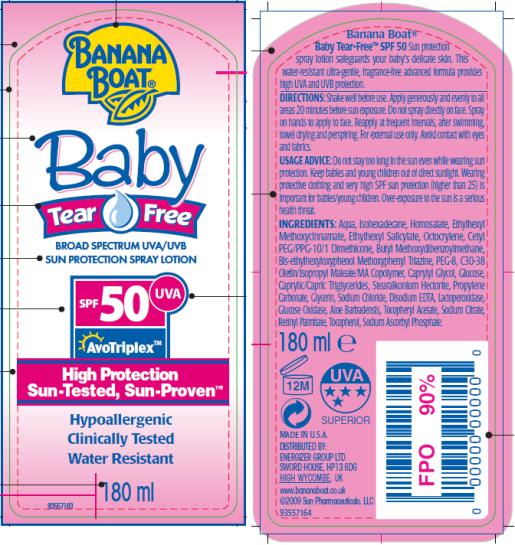 DRUG LABEL: Banana Boat Baby Tear Free Lotion SPF 50
NDC: 17630-2006 | Form: SPRAY
Manufacturer: Accra-Pac, Inc.
Category: otc | Type: HUMAN OTC DRUG LABEL
Date: 20100321

ACTIVE INGREDIENTS: HOMOSALATE 0.1 mL/1 mL; OCTINOXATE 0.075 mL/1 mL; OCTISALATE 0.05 mL/1 mL; OCTOCRYLENE 0.05 mL/1 mL; AVOBENZONE 0.03 mL/1 mL
INACTIVE INGREDIENTS: BEMOTRIZINOL; CAPRYLYL GLYCOL; MEDIUM-CHAIN TRIGLYCERIDES; PROPYLENE CARBONATE; GLYCERIN; SODIUM CHLORIDE; EDETATE DISODIUM; GLUCOSE OXIDASE; .ALPHA.-TOCOPHEROL ACETATE, D-; SODIUM CITRATE; VITAMIN A PALMITATE; SODIUM ASCORBYL PHOSPHATE; ALOE VERA LEAF; ALOE VERA LEAF

Banana Boat Baby Tear Free Spray Lotion SPF 50

ACTIVE INGREDIENTS:

Homosalate 0.1 mL / 1mL

Octinoxate 0.075 mL / 1mL

Octisalate 0.05 mL / 1mL

Octocrylene 0.05 mL / 1mL

Avobenzone 0.03 mL / 1mL

DIRECTIONS:

Shake well before use. Apply generously and evenly to all areas 20 minutes before sun exposure. Do not spray directly on face. Spray on hands to apply to face. Reapply at frequent intervals, after swimming, towel drying and perspiring. For external use only. Avoid contact with eyes and fabrics.

USAGE ADVICE:

Do not stay too long in the sun even while wearing sun protection. Keep babies and young children out of direct sunlight. Wearing protective clothing and very high SPF sun protection (higher than 25) is important for babies/young children. Over-exposure to the sun is a serious health threat.

INGREDIENTS:

Aqua, Isohexadecane, Homosalate, Ethylhexyl Methoxycinnamate, Ethylhexyl Salicylate, Octocrylene, Cetyl PEG/PPG-10/1 Dimethicone, Butyl Methoxydibenzoylmethane, Bis-ethylhexyloxyphenol Methoxyphenyl Triazine, PEG-8, C30-38 Olefin/Isopropyl Maleate/MA Copolymer, Caprylyl Glycol, Glucose, Caprylic/Capric Triglycerides, Stearalkonium Hectorite, Propylene Carbonate, Glycerin, Sodium Chloride, Disodium EDTA, Lactoperoxidase, Glucose Oxidase, Aloe Barbadensis, Tocopheryl Acetate, Sodium Citrate, Retinyl Palmitate, Tocopherol, Sodium Ascorbyl Phosphate.

MADE IN U.S.A.

DISTRIBUTED BY:
ENERGIZER GROUP LTD
SWORD HOUSE, HP13 6DG
HIGH WYCOMBE, UK
www.bananaboat.co.uk

Manufactured by:
Accra Pac, Inc (dba KIK Custom Products)

PRINCIPAL DISPLAY PANEL

Banana
Boat®
Baby
Tear Free
BROAD SPECTRUCM UVA/UVB
SUN PROTECTION SPRAY LOTION
SPF 50 UVA
AvoTriplex TM
High Protection
Sun-Tested, Sun-Proven TM
Hypoallergenic
Clinically Tested
Water Resistant
180 ml